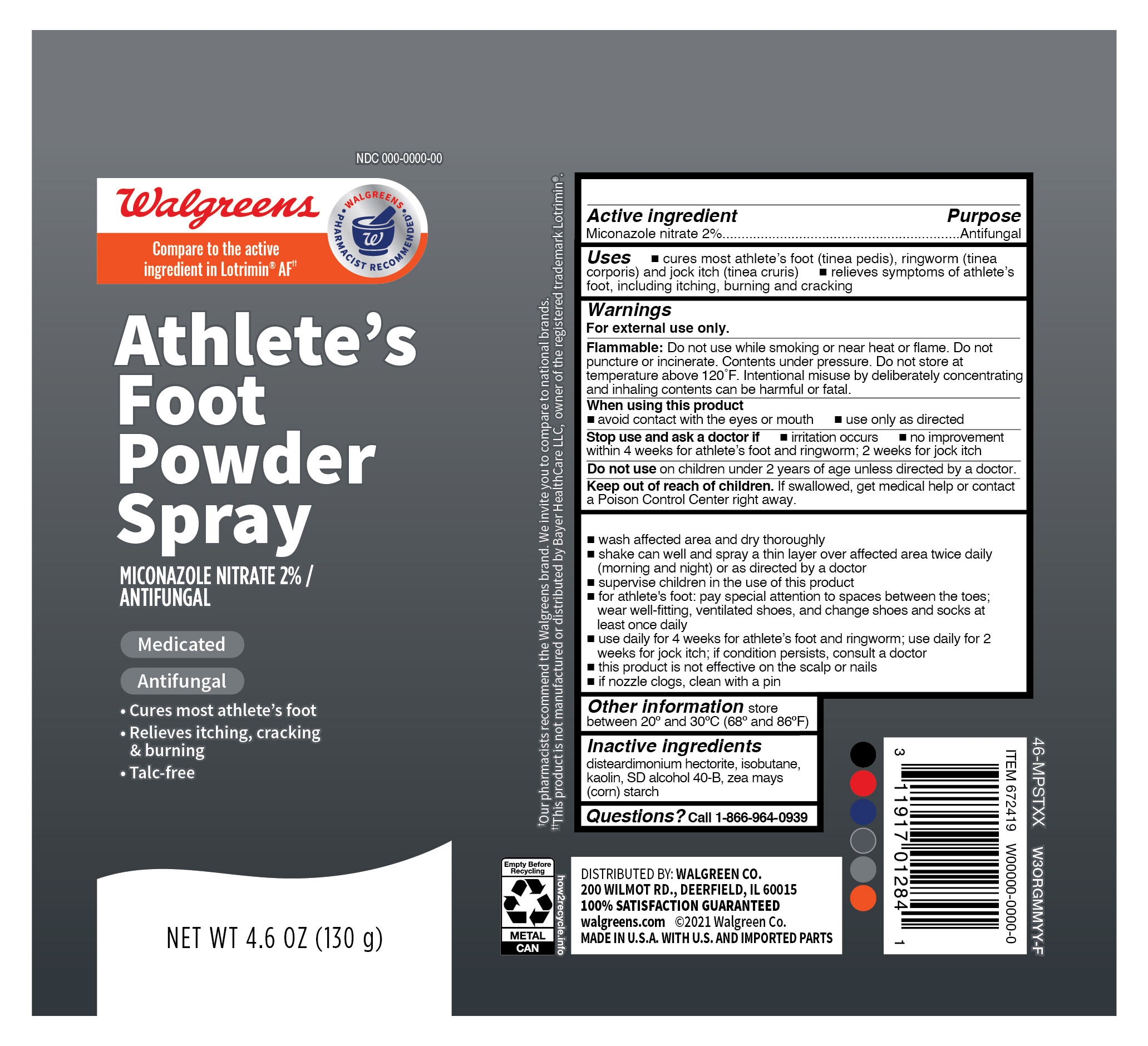 DRUG LABEL: Miconazole Nitrate
NDC: 0363-7418 | Form: AEROSOL, SPRAY
Manufacturer: Walgreens Company
Category: otc | Type: HUMAN OTC DRUG LABEL
Date: 20251205

ACTIVE INGREDIENTS: MICONAZOLE NITRATE 2.6 g/130 g
INACTIVE INGREDIENTS: DISTEARDIMONIUM HECTORITE; KAOLIN; ISOBUTANE; STARCH, CORN; ALCOHOL

Walgreens Athlete's Foot Powder Spray

Active ingredient

Miconozole nitrate2%

Purpose

Antifungal

Uses

- cures most athlete's foot (tinea pedis), ringworm (tinea corporis) and jock itch (tinea cruris)
- relieves symtoms of athlete's foot, including itching, burning and cracking

Warnings

For external use only.

Flammable:

Do not use while smoking or near heat or flame. Do not puncture or incinerate. Contents under pressure. Do not store at temperature above 120o F. Intentional misuse by deliberately concentrating and inhaling contents can be harmful or fatal.

When using this product

- avoid contact with the eyes or mouth
- use only as directed

Stop use and ask a doctor if

- irritation occurs
- no improvement within 4 weeks for athlete's foot and ringworm; 2 weeks for jock itch

Do not use

on children under 2 years of age unless directed by a doctor

Keep out of reach of children

If swallowed, get medical help or contact a Poison Control Center right away.

Directions

- wash affected area and dry thoroughly
- shake can well and spray a thin layer over affected area twice daily (morning and night) or as directed by a doctor
- supervise children in the use of this product
- for athlete's foot: pay special attention to spaces between toes; wear well-fitting, ventilated shoes, and change shoes and socks at least once daily
- use daily for 4 weeks for athlete's foot and ringworm; use daily for 2 weeks for jock itch; if condition persists, consult a doctor
- this product is not effective on the scalp or nails
- if nozzle clogs, clean with a pin

Other infomation

Store between 20o and 30o C (68o and 86o F)

Inactive ingredients

disteardimonium hectorite, isobutane, kaolin, SD alcohol 40-B, zea mays (corn) starch

Questions

Call 1-866-964-0939

PRINCIPAL DISPLAY PANEL

Walgreens

Athlete's

Foot

Powder

Spray

MICONAZOLE NITRATE 2%/

ANTIFUNGAL

Medicated

Antifungal

- Cures most athlete's foot
- Relieves itching, cracking

& burning

- Talc-free

NET WT 4.6 OZ (130 g)